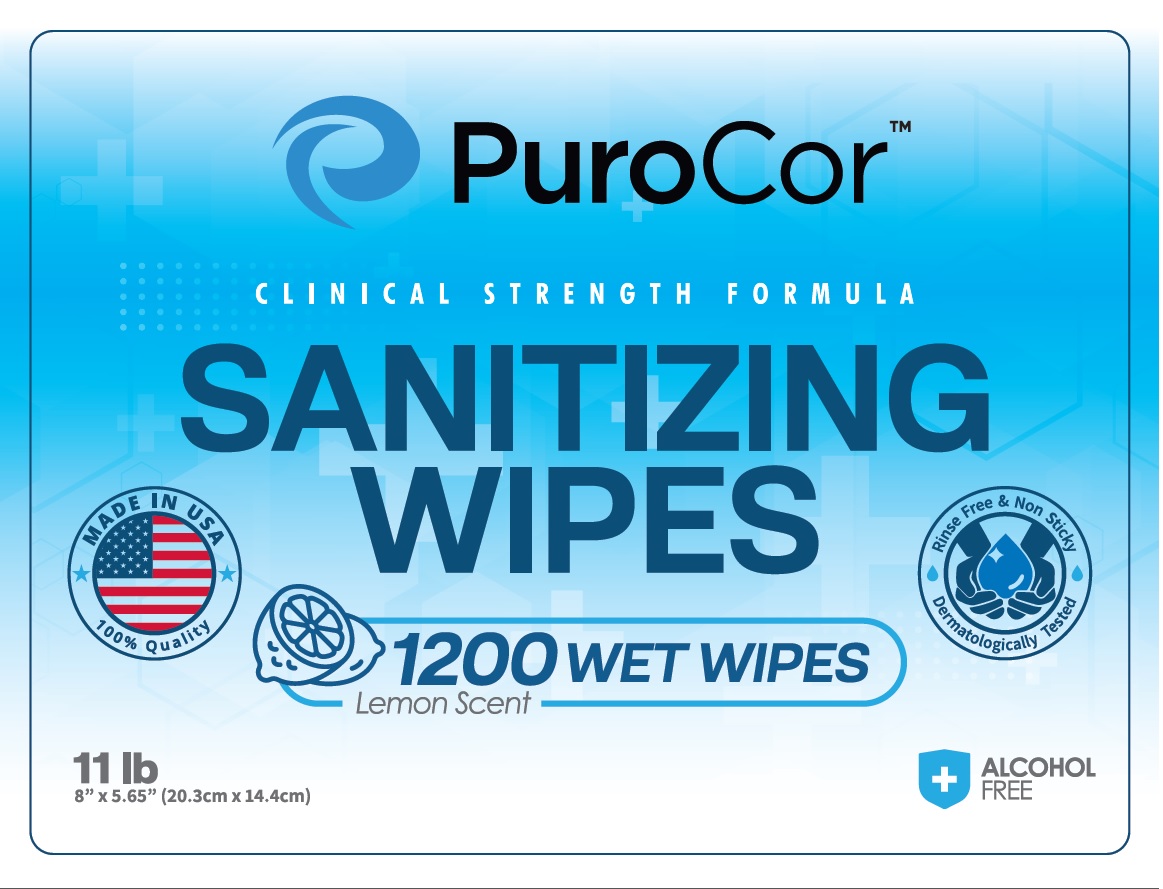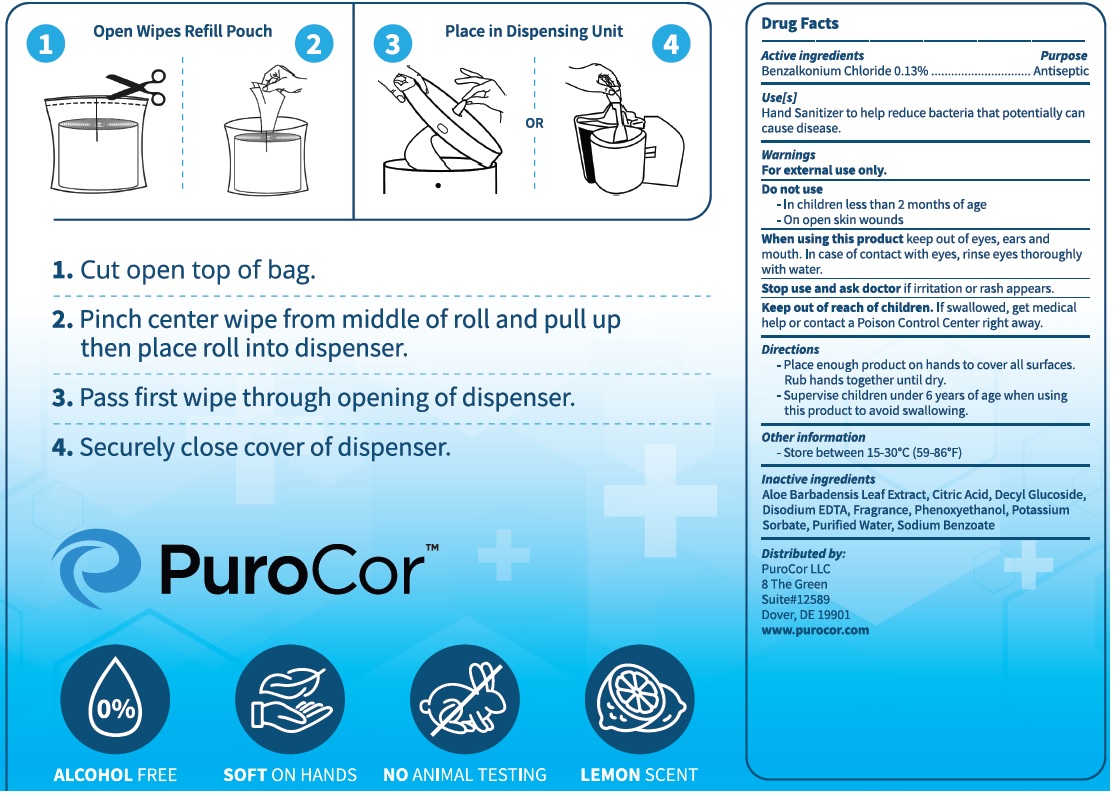 DRUG LABEL: Benzalkonium Chloride
NDC: 82663-001 | Form: CLOTH
Manufacturer: Purocor LLC
Category: otc | Type: HUMAN OTC DRUG LABEL
Date: 20221129

ACTIVE INGREDIENTS: BENZALKONIUM CHLORIDE 0.013 mg/100 mg
INACTIVE INGREDIENTS: DECYL GLUCOSIDE; ALOE VERA LEAF; SODIUM BENZOATE; PHENOXYETHANOL; POTASSIUM SORBATE; WATER; EDETATE DISODIUM ANHYDROUS; CITRIC ACID MONOHYDRATE

Sanitizing Wipes

Active ingredients

Benzalkonium Chloride 0.13%

Purpose

Antiseptic

Use(s)

Hand Sanitizer to help reduce bacteria that potentially can cause disease.

Warnings

For external use only.

Do not use

- In children less than 2 months of age
- On open skin wounds

When using this product

keep out of eyes, ears and mouth. In case of contact with eyes, rinse eyes thoroughly with water.

Stop use and ask doctor

If irritation or rash appears.

Keep out of reach of children.

If swallowed, get medical help or contact a Poison Control Center right away.

Directions

- Place enough product on hands to cover all surfaces. Rub hands together until dry.
- Supervise children under 6 years of age when using this product to avoid swallowing.

Other information

- Store between 15-30ºC (59-86ºF)

Inactive ingredients

Aloe Barbadensis Leaf Extract, Citric Acid, Decyl Glucoside, Disodium EDTA, Fragrance, Phenoxyethanol, Potassium Sorbate, Purified Water, Sodium Benzoate

Principal Display Panel

PuroCor

CLINICAL STRENGTH FORMULA

SANITIZING

WIPES

1200 WET WIPES

Lemon Scent

ALCOHOL

FREE

8" X 5.65" (20.3cm x 14.4cm)